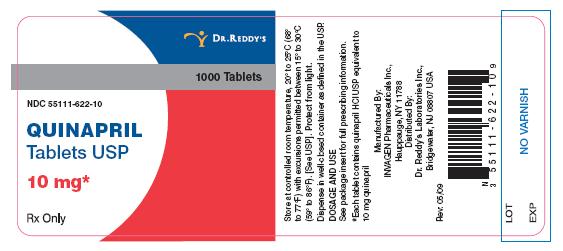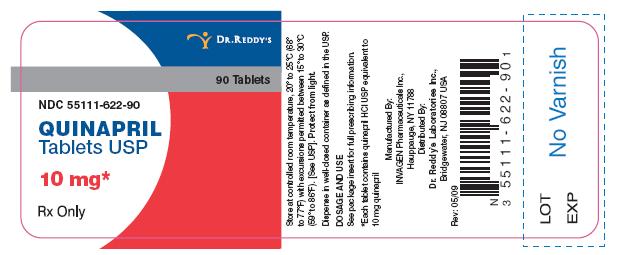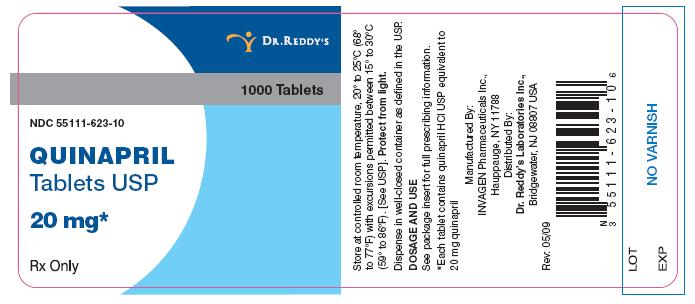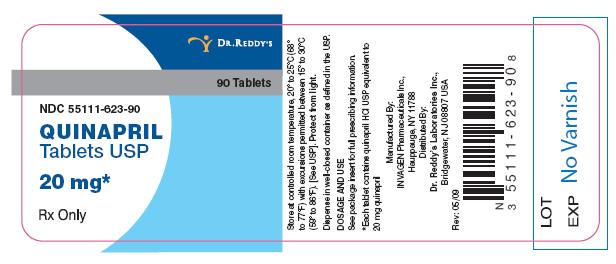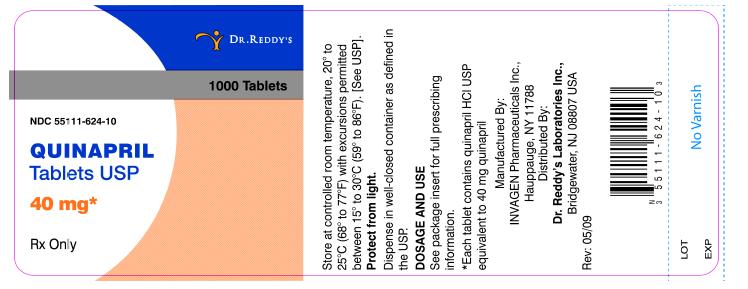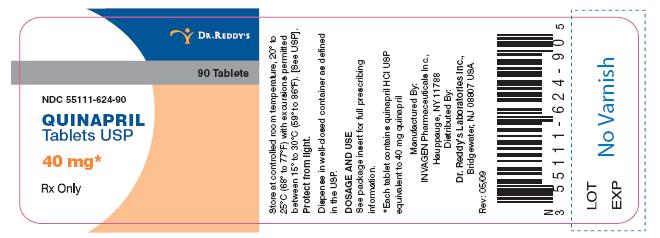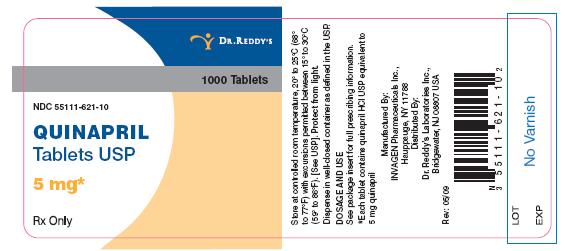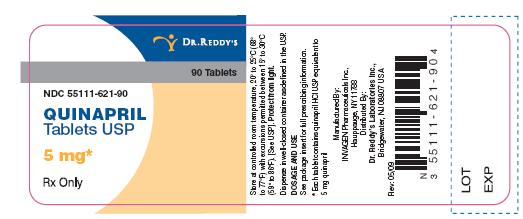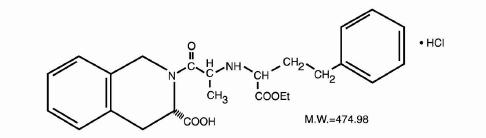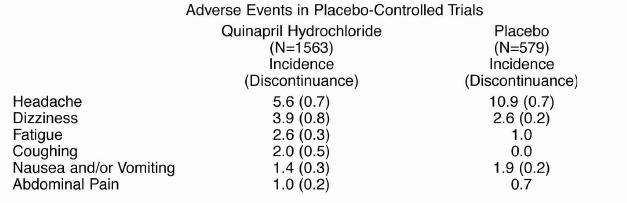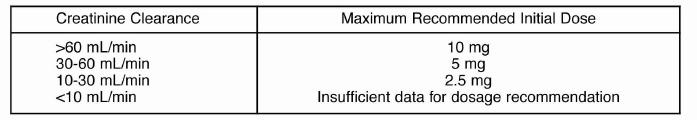 DRUG LABEL: Quinapril
NDC: 55111-621 | Form: TABLET
Manufacturer: Dr.Reddy's Laboratories Limited
Category: prescription | Type: HUMAN PRESCRIPTION DRUG LABEL
Date: 20090909

ACTIVE INGREDIENTS: quinapril hydrochloride 5 mg/1 1
INACTIVE INGREDIENTS: lactose monohydrate; magnesium carbonate; magnesium stearate; crospovidone; polyethylene glycol; ferric oxide red; ferric oxide yellow; povidone; hypromellose; titanium dioxide

Quinapril Tablets

BOXED WARNING

USE IN PREGNANCY

When used in pregnancy during the second and third trimesters, ACE inhibitors can cause injury and even death to the developing fetus. When pregnancy is detected, quinapril tablets should be discontinued as soon as possible. See WARNINGS, Fetal/Neonatal Morbidity and Mortality

DESCRIPTION

Quinapril hydrochloride USP is the hydrochloride salt of quinapril, the ethyl ester of a non-sulfhydryl,angiotensin-converting enzyme (ACE) inhibitor, quinaprilat.

Quinapril hydrochloride USP is chemically described as [3S-[2[R*(R*)], 3R*]]-2-[2-[[1(ethoxycarbonyl)-3-phenylpropyl]amino]-1-oxopropyl]-1 ,2,3,4-tetrahydro-3-isoquinolinecarboxylicacid, monohydrochloride. Its empirical formula is C2SH30N20s -HCI and its structural formula is:

Quinapril hydrochloride USP is a white to off-white amorphous powder that is freely soluble inaqueous solvents.

Quinapril Tablets USP contain quinapril hydrochloride equivalent to 5 mg, 10 mg, 20 mg, or 40 mgof quinapril for oral administration.

Each tablet also contains lactose monohydrate, magnesium carbonate, magnesium stearate,crospovidone, povidone and opadry brown (hypromellose, titanium dioxide, ironoxide and macrogol).

CLINICAL PHARMACOLOGY

Mechanism of Action

Quinapril is deesterified to the principal metabolite, quinaprilat, which is aninhibitor of ACE activity in human subjects and animals. ACE is a peptidyl dipeptidase that catalyzesthe conversion of angiotensin I to the vasoconstrictor, angiotensin II. The effect of quinapril inhypertension appears to result primarily from the inhibition of circulating and tissue ACE activity,thereby reducing angiotensin II formation. Quinapril inhibits the elevation in blood pressure causedby intravenously administered angiotensin I, but has no effect on the pressor response toangiotensin II, norepinephrine or epinephrine. Angiotensin II also stimulates the secretion ofaldosterone from the adrenal cortex, thereby facilitating renal sodium and fluid reabsorption.Reduced aldosterone secretion by quinapril may result in a small increase in serum potassium. Incontrolled hypertension trials, treatment with quinapril hydrochloride alone resulted in meanincreases in potassium of 0.07 mmol/L (see PRECAUTIONS). Removal of angiotensin II negativefeedback on renin secretion leads to increased plasma renin activity (PRA).

While the principal mechanism of antihypertensive effect is thought to be through the reninangiotensin-aldosterone system, quinapril exerts antihypertensive actions even in patients with lowrenin hypertension. Quinapril hydrochloride was an effective antihypertensive in all races studied,although it was somewhat less effective in blacks (usually a predominantly low renin group) than innonblacks. ACE is identical to kininase II, an enzyme that degrades bradykinin, a potent peptidevasodilator; whether increased levels of bradykinin playa role in the therapeutic effect of quinaprilremains to be elucidated.

Pharmacokinetics and Metabolism

Following oral administration, peak plasma quinaprilconcentrations are observed within one hour. Based on recovery of quinapril and its metabolites inurine, the extent of absorption is at least 60%. The rate and extent of quinapril absorption arediminished moderately (approximately 25 to 30%) when quinapril hydrochloride tablets areadministered during a high-fat meal. Following absorption, quinapril is deesterified to its major activemetabolite, quinaprilat (about 38% of oral dose), and to other minor inactive metabolites. Followingmultiple oral dosing of quinapril hydrochloride, there is an effective accumulation half-life ofquinaprilat of approximately 3 hours, and peak plasma quinaprilat concentrations are observedapproximately 2 hours post-dose. Quinaprilat is eliminated primarily by renal excretion, up to 96% ofan IV dose, and has an elimination half-life in plasma of approximately 2 hours and a prolongedterminal phase with a half-life of 25 hours. The pharmacokinetics of quinapril and quinaprilat arelinear over a single-dose range of 5 to 80 mg doses and 40 to 160 mg in multiple daily doses.Approximately 97% of either quinapril or quinaprilat circulating in plasma is bound to proteins.

In patients with renal insufficiency, the elimination half-life of quinaprilat increases as creatinineclearance decreases. There is a linear correlation between plasma quinaprilat clearance andcreatinine clearance. In patients with end-stage renal disease, chronic hemodialysis or continuousambulatory peritoneal dialysis has little effect on the elimination of quinapril and quinaprilat.Elimination of quinaprilat may be reduced in elderly patients (≥65 years) and in those with heartfailure; this reduction is attributable to decrease in renal function (see DOSAGE ANDADMINISTRATION). Quinaprilat concentrations are reduced in patients with alcoholic cirrhosis dueto impaired deesterification of quinapril. Studies in rats indicate that quinapril and its metabolites donot cross the blood-brain barrier.

Pharmacodynamics and Clinical Effects

Hypertension

Single doses of 20 mg of quinapril hydrochloride provide over 80% inhibition ofplasma ACE for 24 hours. Inhibition of the pressor response to angiotensin I is shorter-lived, with a20 mg dose giving 75% inhibition for about 4 hours, 50% inhibition for about 8 hours, and 20%inhibition at 24 hours. With chronic dosing, however, there is substantial inhibition of angiotensin IIlevels at 24 hours by doses of 20 to 80 mg.

Administration of 10 to 80 mg of quinapril hydrochloride to patients with mild to severe hypertensionresults in a reduction of sitting and standing blood pressure to about the same extent with minimaleffect on heart rate. Symptomatic postural hypotension is infrequent although it can occur in patientswho are salt-and/or volume-depleted (see WARNINGS). Antihypertensive activity commences within1 hour with peak effects usually achieved by 2 to 4 hours after dosing. During chronic therapy, mostof the blood pressure lowering effect of a given dose is obtained in 1 to 2 weeks. In multiple-dosestudies, 10 to 80 mg per day in single or divided doses lowered systolic and diastolic blood pressurethroughout the dosing interval, with a trough effect of about 5 to 11/3 to 7 mm Hg. The trough effectrepresents about 50% of the peak effect. While the dose-response relationship is relatively flat,doses of 40 to 80 mg were somewhat more effective at trough than 10 to 20 mg, and twice dailydosing tended to give a somewhat lower trough blood pressure than once daily dosing with the sametotal dose. The antihypertensive effect of quinapril hydrochloride continues during long-term therapy,with no evidence of loss of effectiveness.

Hemodynamic assessments in patients with hypertension indicate that blood pressure reductionproduced by quinapril is accompanied by a reduction in total peripheral resistance and renalvascular resistance with little or no change in heart rate, cardiac index, renal blood flow, glomerularfiltration rate, or filtration fraction.

Use of quinapril hydrochloride with a thiazide diuretic gives a blood pressure lowering effect greaterthan that seen with either agent alone.

In patients with hypertension, quinapril hydrochloride 10 to 40 mg was similar in effectiveness tocaptopril, enalapril, propranolol, and thiazide diuretics.

Therapeutic effects appear to be the same for elderly (≥65 years of age) and younger adult patientsgiven the same daily dosages, with no increase in adverse events in elderly patients.

INDICATIONS AND USAGE

Hypertension

Quinapril hydrochloride is indicated for the treatment of hypertension. It may be used alone or incombination with thiazide diuretics.

In using quinapril hydrochloride, consideration should be given to the fact that another angiotensinconvertingenzyme inhibitor, captopril, has caused agranulocytosis, particularly in patients with renalimpairment or collagen vascular disease. Available data are insufficient to show that quinaprilhydrochloride does not have a similar risk (see WARNINGS).

Angioedema in black patients

Black patients receiving ACE inhibitor monotherapy have beenreported to have a higher incidence of angioedema compared to non-blacks. It should also be notedthat in controlled clinical trials ACE inhibitors have an effect on blood pressure that is less in blackpatients than in non-blacks.

CONTRAINDICATIONS

Quinapril hydrochloride is contraindicated in patients who are hypersensitive to this product and inpatients with a history of angioedema related to previous treatment with an ACE inhibitor.

WARNINGS

Anaphylactoid and Possibly Related Reactions

Presumably because angiotensin-converting inhibitors affect the metabolism of eicosanoids andpolypeptides, including endogenous bradykinin, patients receiving ACE inhibitors (including quinapril hydrochloride) may be subject to a variety of adverse reactions, some of them serious.

Head and Neck Angioedema

Angioedema of the face, extremities, lips, tongue, glottis, and larynxhas been reported in patients treated with ACE inhibitors and has been seen in 0.1% of patientsreceiving quinapril hydrochloride.

In two similarly sized U.S. postmarketing trials that, combined, enrolled over 3,000 black patients andover 19,000 non-blacks, angioedema was reported in 0.30% and 0.55% of blacks (in study 1 and 2respectively) and 0.39% and 0.17% of non-blacks.

Angioedema associated with laryngeal edema can be fatal. If laryngeal stridor or angioedema of theface, tongue, or glottis occurs, treatment with quinapril hydrochloride should be discontinuedimmediately, the patient treated in accordance with accepted medical care, and carefully observeduntil the swelling disappears. In instances where swelling is confined to the face and lips, thecondition generally resolves without treatment; antihistamines may be useful in relieving symptoms.Where there is involvement of the tongue, glottis, or larynx likely to cause airway obstruction,emergency therapy including, but not limited to, subcutaneous epinephrine solution 1:1000(0.3 to 0.5 mL) should be promptly administered (see ADVERSE REACTIONS).

Intestinal Angioedema

Intestinal angioedema has been reported in patients treated with ACEinhibitors. These patients presented with abdominal pain (with or without nausea or vomiting); insome cases there was no prior history of facial angioedema and C-1 esterase levels were normal.The angioedema was diagnosed by procedures including abdominal CT scan or ultrasound, or atsurgery, and symptoms resolved after stopping the ACE inhibitor. Intestinal angioedema should beincluded in the differential diagnosis of patients on ACE inhibitors presenting with abdominal pain.

Patients with a history of angioedema unrelated to ACEinhibitor therapy may be at increased risk of angioedema while receiving an ACE inhibitor (see also CONTRAINDICATIONS).

Anaphylactoid reactions during desensitization

Two patients undergoing desensitizingtreatment with hymenoptera venom while receiving ACE inhibitors sustained life-threateninganaphylactoid reactions. In the same patients, these reactions were avoided when ACE inhibitorswere temporarily withheld, but they reappeared upon inadvertent rechallenge.

Anaphylactoid reactions during membrane exposure

Anaphylactoid reactions have beenreported in patients dialyzed with high-flux membranes and treated concomitantly with an ACEinhibitor. Anaphylactoid reactions have also been reported in patients undergoing low-densitylipoprotein apheresis with dextran sulfate absorption.

Hepatic Failure

Rarely, ACE inhibitors have been associated with a syndrome that starts withcholestatic jaundice and progresses to fulminant hepatic necrosis and (sometimes) death. Themechanism of this syndrome is not understood. Patients receiving ACE inhibitors who developjaundice or marked elevations of hepatic enzymes should discontinue the ACE inhibitor and receiveappropriate medical follow-up.

Hypotension

Excessive hypotension is rare in patients with uncomplicated hypertension treatedwith quinapril hydrochloride alone. Patients with heart failure given quinapril hydrochloride commonlyhave some reduction in blood pressure, but discontinuation of therapy because of continuingsymptomatic hypotension usually is not necessary when dosing instructions are followed. Cautionshould be observed when initiating therapy in patients with heart failure (see DOSAGE ANDADMINISTRATION). In controlled studies, syncope was observed in 0.4% of patients (N=3203); thisincidence was similar to that observed for captopril (1 %) and enalapril (0.8%).

Patients at risk of excessive hypotension, sometimes associated with oliguria and/or progressiveazotemia, and rarely with acute renal failure and/or death, include patients with the followingconditions or characteristics: heart failure, hyponatremia, high dose diuretic therapy, recent intensivediuresis or increase in diuretic dose, renal dialysis, or severe volume and/or salt depletion of anyetiology. It may be advisable to eliminate the diuretic (except in patients with heart failure), reducethe diuretic dose or cautiously increase salt intake (except in patients with heart failure) beforeinitiating therapy with quinapril hydrochloride in patients at risk for excessive hypotension who areable to tolerate such adjustments.

In patients at risk of excessive hypotension, therapy with quinapril hydrochloride should be startedunder close medical supervision. Such patients should be followed closely for the first two weeks oftreatment and whenever the dose of quinapril hydrochloride and/or diuretic is increased. Similarconsiderations may apply to patients with ischemic heart or cerebrovascular disease in whom anexcessive fall in blood pressure could result in a myocardial infarction or a cerebrovascular accident.

If excessive hypotension occurs, the patient should be placed in the supine position and, ifnecessary, receive an intravenous infusion of normal saline. A transient hypotensive response is nota contraindication to further doses of quinapril hydrochloride, which usually can be given withoutdifficulty once the blood pressure has stabilized. If symptomatic hypotension develops, a dosereduction or discontinuation of quinapril hydrochloride or concomitant diuretic may be necessary.

Neutropenia/Agranulocytosis

Another ACE inhibitor, captopril, has been shown to causeagranulocytosis and bone marrow depression rarely in patients with uncomplicated hypertension,but more frequently in patients with renal impairment, especially if they also have a collagen vasculardisease, such as systemic lupus erythematosus or scleroderma. Agranulocytosis did occur duringquinapril hydrochloride treatment in one patient with a history of neutropenia during previouscaptopril therapy. Available data from clinical trials of quinapril hydrochloride are insufficient to showthat, in patients without prior reactions to other ACE inhibitors, quinapril hydrochloride does notcause agranulocytosis at similar rates. As with other ACE inhibitors, periodic monitoring of whiteblood cell counts in patients with collagen vascular disease and/or renal disease should beconsidered.

Fetal/Neonatal Morbidity and Mortality

ACE inhibitors can cause fetal and neonatal morbidity anddeath when administered to pregnant women. Several dozen cases have been reported in the worldliterature. When pregnancy is detected, ACE inhibitors should be discontinued as soon as possible.

The use of ACE inhibitors during the second and third trimesters of pregnancy has been associatedwith fetal and neonatal injury, including hypotension, neonatal skull hypoplasia, anuria, reversible orirreversible renal failure, and death. Oligohydramnios has also been reported, presumably resultingfrom decreased fetal renal function; oligohydramnios in this setting has been associated with fetallimb contractures, craniofacial deformation, and hypoplastic lung development. Prematurity,intrauterine growth retardation, and patent ductus arteriosus have also been reported, although it isnot clear whether these occurrences were due to the ACE inhibitor exposure.

These adverse effects do not appear to have resulted from intrauterine ACE inhibitor exposure thathas been limited to the first trimester. Mothers whose embryos and fetuses are exposed to ACEinhibitors only during the first trimester should be so informed. Nonetheless, when patients becomepregnant, physicians should make every effort to discontinue the use of quinapril hydrochloride assoon as possible.

Rarely (probably less often than once in every thousand pregnancies), no alternative to ACEinhibitors will be found. In these rare cases, the mothers should be apprised of the potential hazardsto their fetuses, and serial ultrasound examinations should be performed to assess the intraamnioticenvironment.

If oligohydramnios is observed, quinapril hydrochloride should be discontinued unless it isconsidered lifesaving for the mother. Contraction stress testing (CST), a non-stress test (NST), orbiophysical profiling (BPP) may be appropriate, depending upon the week of pregnancy. Patientsand physicians should be aware, however, that oligohydramnios may not appear until after the fetushas sustained irreversible injury.

Infants with histories of in utero exposure to ACE inhibitors should be closely observed forhypotension, oliguria, and hyperkalemia. If oliguria occurs, attention should be directed towardsupport of blood pressure and renal perfusion. Exchange transfusion or dialysis may be required asa means of reversing hypotension and/or substituting for disordered renal function. Removal ofquinapril hydrochloride, which crosses the placenta, from the neonatal circulation is not significantlyaccelerated by these means.

No teratogenic effects of quinapril hydrochloride were seen in studies of pregnant rats and rabbits.On a mg/kg basis, the doses used were up to 180 times (in rats) and one time (in rabbits) themaximum recommended human dose.

PRECAUTIONS

General

Impaired renal function

As a consequence of inhibiting the renin-angiotensinaldosterone system,changes in renal function may be anticipated in susceptible individuals. In patients with severe heartfailure whose renal function may depend on the activity of the renin-angiotensinaldosterone system,treatment with ACE inhibitors, including quinapril hydrochloride, may be associated with oliguriaand/or progressive azotemia and rarely acute renal failure and/or death.

In clinical studies in hypertensive patients with unilateral or bilateral renal artery stenosis, increasesin blood urea nitrogen and serum creatinine have been observed in some patients following ACEinhibitor therapy. These increases were almost always reversible upon discontinuation of the ACEinhibitor and/or diuretic therapy. In such patients, renal function should be monitored during the firstfew weeks of therapy.

Some patients with hypertension or heart failure with no apparent preexisting renal vascular diseasehave developed increases in blood urea and serum creatinine, usually minor and transient,especially when quinapril hydrochloride has been given concomitantly with a diuretic. This is morelikely to occur in patients with preexisting renal impairment. Dosage reduction and/or discontinuationof any diuretic and/or quinapril hydrochloride may be required.

Evaluation of patients with hypertension or heart failure should always include assessmentof renal function (see DOSAGE AND ADMINISTRATION).

Hyperkalemia and potassium-sparing diuretics: In clinical trials, hyperkalemia (serum potassium≥5.8 mmol/L) occurred in approximately 2% of patients receiving quinapril hydrochloride. In mostcases, elevated serum potassium levels were isolated values which resolved despite continuedtherapy. Less than 0.1% of patients discontinued therapy due to hyperkalemia. Risk factors for thedevelopment of hyperkalemia include renal insufficiency, diabetes mellitus, and the concomitant useof potassium-sparing diuretics, potassium supplements, and/or potassium containing saltsubstitutes, which should be used cautiously, if at all, with quinapril hydrochloride (see PRECAUTIONS, Drug Interactions).

Cough

Presumably due to the inhibition of the degradation of endogenous bradykinin, persistentnon-productive cough has been reported with all ACE inhibitors, always resolving afterdiscontinuation of therapy. ACE inhibitor-induced cough should be considered in the differentialdiagnosis of cough.

Surgery/anesthesia

In patients undergoing major surgery or during anesthesia with agents thatproduce hypotension, quinapril hydrochloride will block angiotensin II formation secondary tocompensatory renin release. If hypotension occurs and is considered to be due to this mechanism,it can be corrected by volume expansion.

Information for Patients

Pregnancy

Female patients of childbearing age should be told about the consequences of secondandthird-trimester exposure to ACE inhibitors, and they should also be told that theseconsequences do not appear to have resulted from intrauterine ACE-inhibitor exposure that hasbeen limited to the first trimester. These patients should be asked to report pregnancies to theirphysicians as soon as possible.

Angioedema

Angioedema, including laryngeal edema can occur with treatment with ACEinhibitors, especially following the first dose. Patients should be so advised and told to reportimmediately any signs or symptoms suggesting angioedema (swelling of face extremities, eyes, lips,tongue, difficulty in swallowing or breathing: and to stop taking the drug until they have consultedwith their physician (see WARNINGS).

Symptomatic hypotension

Patients should be cautioned that light-headedness can occur,especially during the first few days of quinapril hydrochloride therapy, and that it should be reportedto a physician. If actual syncope occurs, patients should be told to not take the drug until they haveconsulted with their physician (see WARNINGS).

All patients should be cautioned that inadequate fluid intake or excessive perspiration, diarrhea, orvomiting can lead to an excessive fall in blood pressure because of reduction in fluid volume, withthe same consequences of lightheadedness and possible syncope.

Patients planning to undergo any surgery and/or anesthesia should be told to inform their physicianthat they are taking an ACE inhibitor.

Hyperkalemia

Patients should be told not to use potassium supplements or salt substitutescontaining potassium without consulting their physician (see PRECAUTIONS).

Neutropenia

Patients should be told to report promptly any indication of infection (eg, sore throat,fever) which could be a sign of neutropenia.

NOTE: As with many other drugs, certain advice to patients being treated with quinaprilhydrochloride is warranted. This information is intended to aid in the safe and effective use of thismedication. It is not a disclosure of all possible adverse or intended effects.

Drug Interactions

Concomitant diuretic therapy

As with other ACE inhibitors, patients on diuretics, especially thoseon recently instituted diuretic therapy may occasionally experience an excessive reduction of bloodpressure after initiation of therapy with quinapril hydrochloride. The possibility of hypotensive effectswith quinapril hydrochloride may be minimized by either discontinuing the diuretic or cautiouslyincreasing salt intake prior to initiation of treatment with quinapril hydrochloride. If it is not possibleto discontinue the diuretic, the starting dose of quinapril should be reduced (see DOSAGE ANDADMINISTRATION).

Agents increasing serum potassium

Quinapril can attenuate potassium loss caused by thiazidediuretics and increase serum potassium when used alone. If concomitant therapy of quinaprilhydrochloride with potassium-sparing diuretics (eg, spironolactone, triamterene, or amiloride),potassium supplements, or potassium-containing salt substitutes is indicated, they should be usedwith caution along with appropriate monitoring of serum potassium (see PRECAUTIONS).

Tetracycline and other drugs that interact with magnesium

Simultaneous administration oftetracycline with quinapril hydrochloride reduced the absorption of tetracycline by approximately28% to 37%, possibly due to the high magnesium content in quinapril hydrochloride tablets. Thisinteraction should be considered if coprescribing quinapril hydrochloride and tetracycline or otherdrugs that interact with magnesium.

Lithium

Increased serum lithium levels and symptoms of lithium toxicity have been reported inpatients receiving concomitant lithium and ACE inhibitor therapy. These drugs should becoadministered with caution and frequent monitoring of serum lithium levels is recommended. If adiuretic is also used, it may increase the risk of lithium toxicity.

Other agents

Drug interaction studies of quinapril hydrochloride with other agents showed:

- Multiple dose therapy with propranolol or cimetidine has no effect on the pharmacokinetics ofsingle doses of quinapril hydrochloride.
- The anticoagulant effect of a single dose of warfarin (measured by prothrombin time) was notsignificantly changed by quinapril coadministration twice-daily.
- quinapril hydrochloride treatment did not affect the pharmacokinetics of digoxin.
- No pharmacokinetic interaction was observed when single doses of quinapril hydrochloride andhydrochlorothiazide were administered concomitantly.
- Co-administration of multiple 10 mg doses of atorvastatin with 80 mg of quinapril hydrochlorideresulted in no significant change in the steady-state pharmacokinetic parameters of atorvastatin.

Carcinogenesis, Mutagenesis, Impairment of Fertility

Quinapril hydrochloride was not carcinogenic in mice or rats when given in doses up to 75 or100 mg/kg/day (50 to 60 times the maximum human daily dose, respectively, on an mg/kg basis and3.8 to 10 times the maximum human daily dose when based on an mg/m^2 basis) for 104 weeks.Female rats given the highest dose level had an increased incidence of mesenteric lymph nodehemangiomas and skin/subcutaneous lipomas. Neither quinapril nor quinaprilat were mutagenic inthe Ames bacterial assay with or without metabolic activation. Quinapril was also negative in thefollowing genetic toxicology studies: in vitro mammalian cell point mutation, sister chromatidexchange in cultured mammalian cells, micronucleus test with mice, in vitro chromosome aberrationwith V79 cultured lung cells, and in an in vivo cytogenetic study with rat bone marrow. There wereno adverse effects on fertility or reproduction in rats at doses up to 100 mg/kg/day (60 and 10 timesthe maximum daily human dose when based on mg/kg and mg/m^2 , respectively).

Pregnancy: Teratogenic Effects: Pregnancy: Category B.

Pregnancy Categories C (first trimester) and D (second and third trimesters): See WARNINGS,Fetal/Neonatal Morbidity and Mortality.

Nursing Mothers

Because quinapril hydrochloride is secreted in human milk, caution should be exercised when thisdrug is administered to a nursing woman.

Pediatric Use

The safety and effectiveness of quinapril hydrochloride in pediatric patients have not beenestablished.

Geriatric Use

Clinical studies of quinapril hydrochloride did not include sufficient numbers of subjects aged 65 andover to determine whether they respond differently from younger subjects. Other reported clinicalexperience has not identified differences in responses between the elderly and younger patients.

In general, dose selection for an elderly patient should be cautious, usually starting at the low endof the dosing range, reflecting the greater frequency of decreased hepatic, renal or cardiac function,and of concomitant disease or other drug therapy.

This drug is known to be substantially excreted by the kidney, and the risk of toxic reactions to thisdrug may be greater in patients with impaired renal function. Because elderly patients are more likelyto have decreased renal function, care should be taken in dose selection, and it may be useful tomonitor renal function.

Elderly patients exhibited increased area under the plasma concentration time curve and peak levelsfor quinaprilat compared to values observed in younger patients; this appeared to relate todecreased renal function rather than to age itself.

ADVERSE REACTIONS

Hypertension

Quinapril hydrochloride has been evaluated for safety in 4960 subjects and patients. Of these, 3203patients, including 655 elderly patients, participated in controlled clinical trials. Quinaprilhydrochloride has been evaluated for long-term safety in over 1400 patients treated for 1 year ormore.

Adverse experiences were usually mild and transient.

In placebo-controlled trials, discontinuation of therapy because of adverse events was required in4.7% of patients with hypertension.

Adverse experiences probably or possibly related to therapy or of unknown relationship to therapyoccurring in 1% or more of the 1563 patients in placebo-controlled hypertension trials who weretreated with quinapril hydrochloride are shown below.

Hypertension

Clinical adverse experiences probably, possibly, or definitely related, or of uncertain relationship totherapy occurring in 0.5% to 1.0% (except as noted) of the patients with hypertension treated withquinapril hydrochloride (With or without concomitant diuretic) in controlled or uncontrolled trials(N=4847) and less frequent, clinically significant events seen in clinical trials or postmarketingexperience (the rarer events are in italics) include (listed by body system):

General

back pain, malaise, viral infections, anaphylactoid reaction

Cardiovascular

palpitation, vasodilation, tachycardia, heart failure, hyperkalemia, myocardial infarction, cerebrovascular accident, hypertensive crisis, angina pectoris, orthostatic hypotension,cardiac rhythm disturbances, cardiogenic shock

Hematology

hemolytic anemia

Gastrointestinal

flatulence, dry mouth or throat, constipation, gastrointestinal hemorrhage, pancreatitis, abnormal liver function tests, dyspepsia

Nervous/Psychiatric

somnolence, vertigo, syncope, nervousness, depression, insomnia,paresthesia

Integumentary

alopecia, increased sweating, pemphigus, pruritus, exfoliative dermatitis, photosensitivity reaction, dermatopolymyositis

Urogenital

urinary tract infection, impotence, acute renal failure, worsening renal failure

Respiratory

eosinophilic pneumonitis

Other

amblyopia, edema, arthralgia, pharyngitis, agranulocytosis, hepatitis, thrombocytopenia

Fetal/Neonatal Morbidity and Mortality

See WARNINGS , Fetal/Neonatal Morbidity and Mortality

Angioedema

Angioedema has been reported in patients receiving quinapril hydrochloride (0.1 %). Angioedemaassociated with laryngeal edema may be fatal. If angioedema of the face, extremities, lips, tongue,glottis, and/or larynx occurs, treatment with quinapril hydrochloride should be discontinued andappropriate therapy instituted immediately. (See WARNINGS.)

Clinical Laboratory Test Findings

Hematology

(See WARNINGS)

Hyperkalemia

(See PRECAUTIONS)

Creatinine and Blood Urea Nitrogen

Increases (>1.25 times the upper limit of normal) in serumcreatinine and blood urea nitrogen were observed in 2% and 2%, respectively, of all patients treatedwith quinapril hydrochloride alone. Increases are more likely to occur in patients receivingconcomitant diuretic therapy than in those on quinapril hydrochloride alone. These increases oftenremit on continued therapy.

OVERDOSAGE

Doses of 1440 to 4280 mg/kg of quinapril cause significant lethality in mice and rats. No specificinformation is available on the treatment of overdosage with quinapril. The most likely clinicalmanifestation would be symptoms attributable to severe hypotension.

Laboratory determinations of serum levels of quinapril and its metabolites are not widely available,and such determinations have, in any event, no established role in the management of quinapriloverdose.

No data are available to suggest physiological maneuvers (eg, maneuvers to change pH of the urine)that might accelerate elimination of quinapril and its metabolites.

Hemodialysis and peritoneal dialysis have little effect on the elimination of quinapril and quinaprilat.Angiotensin II could presumably serve as a specific antagonist-antidote in the setting of quinapriloverdose, but angiotensin II is essentially unavailable outside of scattered research facilities.Because the hypotensive effect of quinapril is achieved through vasodilation and effectivehypovolemia, it is reasonable to treat quinapril overdose by infusion of normal saline solution.

DOSAGE AND ADMINISTRATION

Hypertension

Monotherapy

The recommended initial dosage of quinapril hydrochloride in patients not ondiuretics is 10 or 20 mg once daily. Dosage should be adjusted according to blood pressureresponse measured at peak (2 to 6 hours after dosing) and trough (predosing). Generally, dosageadjustments should be made at intervals of at least 2 weeks. Most patients have required dosagesof 20, 40, or 80 mg/day, given as a single dose or in two equally divided doses. In some patientstreated once daily, the antihypertensive effect may diminish toward the end of the dosing interval. Insuch patients an increase in dosage or twice daily administration may be warranted. In general,doses of 40 to 80 mg and divided doses give a somewhat greater effect at the end of the dosinginterval.

Concomitant Diuretics

If blood pressure is not adequately controlled with quinapril hydrochloridemonotherapy, a diuretic may be added. In patients who are currently being treated with a diuretic,symptomatic hypotension occasionally can occur following the initial dose of quinapril hydrochloride.To reduce the likelihood of hypotension, the diuretic should, if possible, be discontinued 2 to 3 daysprior to beginning therapy with quinapril hydrochloride (see WARNINGS). Then, if blood pressure isnot controlled with quinapril hydrochloride alone, diuretic therapy should be resumed.

If the diuretic cannot be discontinued, an initial dose of 5 mg quinapril hydrochloride should be usedwith careful medical supervision for several hours and until blood pressure has stabilized.

The dosage should subsequently be titrated (as described above) to the optimal response (seeWARNINGS, PRECAUTIONS, and Drug Interactions).

Renal Impairment

Kinetic data indicate that the apparent elimination half-life of quinaprilatincreases as creatinine clearance decreases. Recommended starting doses, based on clinical andpharmacokinetic data from patients with renal impairment, are as follows:

Patients should subsequently have their dosage titrated (as described above) to the optimalresponse.

Elderly (≥65 years)

The recommended initial dosage of quinapril hydrochloride in elderly patientsis 10 mg given once daily followed by titration (as described above) to the optimal response.

Following the initial dose of quinapril hydrochloride, the patient should be observed under medicalsupervision for at least two hours for the presence of hypotension or orthostatis and, if present, untilblood pressure stabilizes. The appearance of hypotension, orthostatis, or azotemia early in dosetitration should not preclude further careful dose titration. Consideration should be given to reducingthe dose of concomitant diuretics.

DOSE ADJUSTMENTS IN PATIENTS WITH HEART FAILURE AND RENAL IMPAIRMENT OR HYPONATREMIA

Pharmacokinetic data indicate that quinapril elimination is dependent on level of renal function. Inpatients with heart failure and renal impairment, the recommended initial dose of quinaprilhydrochloride is 5 mg in patients with a creatinine clearance above 30 mLlmin and 2.5 mg in patientswith a creatinine clearance of 10 to 30 mL/min. There is insufficient data for dosage recommendationin patients with a creatinine clearance less than 10 mLlmin (see DOSAGE AND ADMINISTRATION,Heart Failure, WARNINGS, and PRECAUTIONS, Drug Interactions).

If the initial dose is well tolerated, quinapril hydrochloride may be administered the following day asa twice daily regimen. In the absence of excessive hypotension or significant deterioration of renalfunction, the dose may be increased at weekly intervals based on clinical and hemodynamicresponse.

HOW SUPPLIED

Quinapril Tablets USP are supplied as follows:

5-mg tablets: brown, round biconvex tablets de-bossed with I on the left side of bisect and G on theright side of bisect and 267 on other.

NDC 55111-621-90 bottles of 90 tablets

NDC 55111-621 -1 a bottles of 1000 tablets

10-mg tablets: brown, round biconvex tablets de-bossed with IG on one side and 268 on other.

NDC 55111-622-90 bottles of 90 tablets

NDC 55111-622-1 a bottles of 1000 tablets

20-mg tablets: brown, round biconvex tablets de-bossed with IG on one side and 269 on other.

NDC 55111-623-90 bottles of 90 tablets

NDC 55111-623-1 a bottles of 1000 tablets

40-mg tablets: brown, oval biconvex tablets de-bossed with IG on one side and 270 on other.

NDC 55111-624-90 bottles of 90 tablets

NDC 55111-624-10 bottles of 1000 tablets

Dispense in well-closed containers as defined in the USP.

Store at controlled room temperature, 20° to 25°C (68° to 7JOF) with excursions permitted betweenPlacebo 15° to 30°C (59° to 86°F). [See USP]. Protect from light.

Manufactured by:

InvaGen Pharmaceuticals, Inc

Hauppauge, NY 11788

Distributed by:

Dr. Reddy's Laboratories Inc.,

Bridgewater, NJ 08807 USA

Rev: 05/09

Labeling

5 mg - Container Labeling

90's count

1000's count

10 mg - Container Labeling

90's count

1000's count

20 mg - Container Labeling

90's count

1000's count

40 mg - Container Labeling

90's count

1000's count